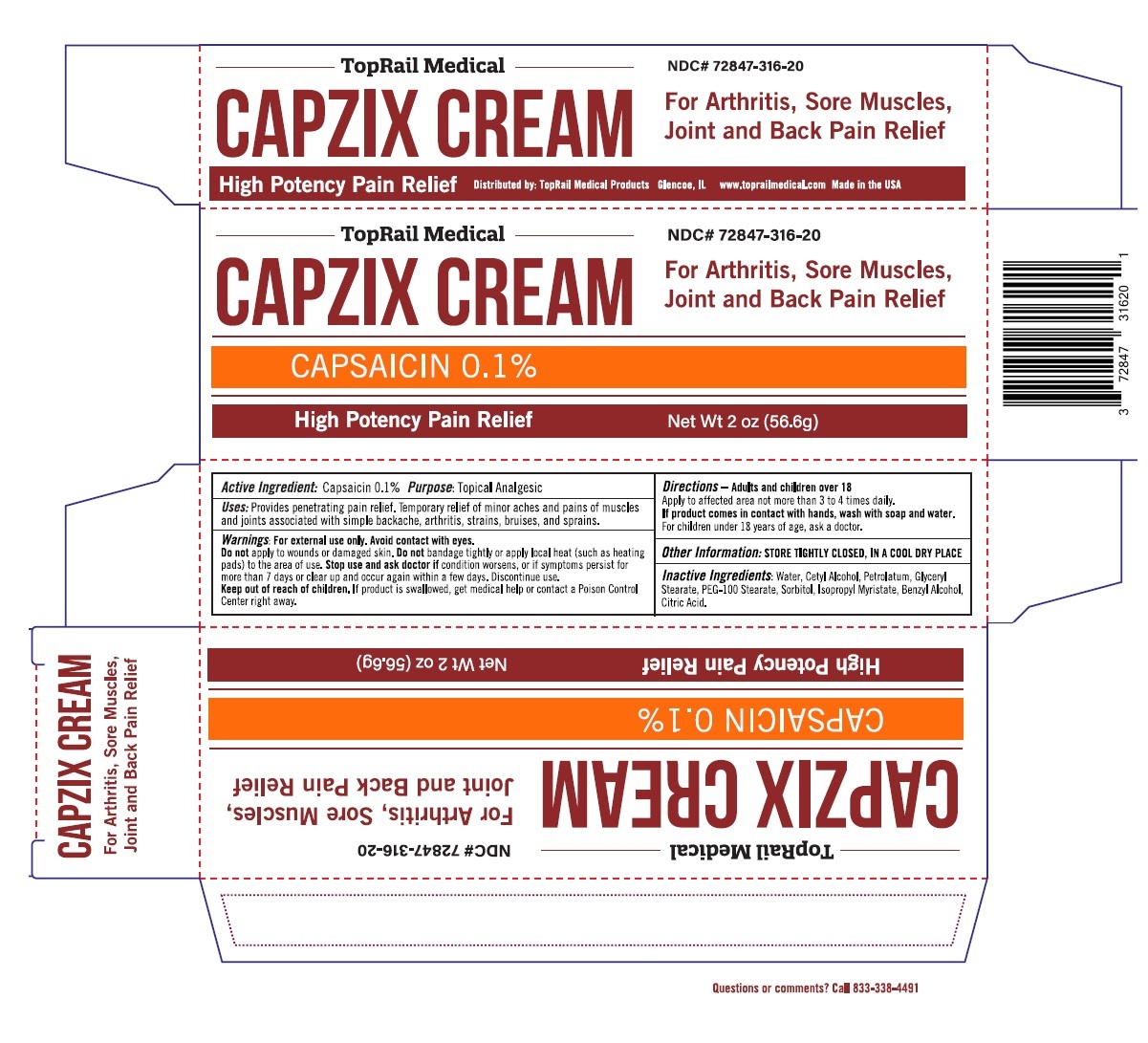 DRUG LABEL: CAPZIX
NDC: 72847-316 | Form: CREAM
Manufacturer: Toprail Chp Llc.
Category: otc | Type: HUMAN OTC DRUG LABEL
Date: 20251112

ACTIVE INGREDIENTS: CAPSAICIN 0.001 g/1 g
INACTIVE INGREDIENTS: WATER; CETYL ALCOHOL; PETROLATUM; GLYCERYL MONOSTEARATE; PEG-100 MONOSTEARATE; SORBITOL; ISOPROPYL MYRISTATE; BENZYL ALCOHOL; CITRIC ACID MONOHYDRATE

CAPZIX CREAM

Active Ingredient:Capsaicin 0.1%

Purpose:Topical Analgesic

INDICATIONS AND USAGE

Uses:Provides penetrating pain relief. Temporary relief of minor aches and pains of muscles and joints associated with simple backache, arthritis, strains, bruises, and sprains.

WARNINGS

Warnings:For external use only. Avoid contact with eyes.
Do notapply to wounds or damaged skin. Do notbandage tightly or apply local heat (such as heating pads) to the area of use. Stop use and ask doctor ifcondition worsens, or if symptoms persist for more than 7 days or clear up and occur again within a few days. Discontinue use.

Keep out of reach of children.If product is swallowed, get medical help or contact a Poison Control Center right away.

DOSAGE AND ADMINISTRATION

Directions– Adults and children over 18
Apply to affected area not more than 3 to 4 times daily.
If product comes in contact with hands, wash with soap and water.
For children under 18 years of age ask a doctor.

Other Information:STORE TIGHTLY CLOSED, IN A COOL DRY PLACE

INACTIVE INGREDIENT

Inactive Ingredients:Water, Cetyl Alcohol, Petrolatum, Glyceryl Stearate, PEG-100 Stearate, Sorbitol, Isopropyl Myristate, Benzyl Alcohol, Citric Acid.

High Potency Pain Relief

For Arthritis, Sore Muscles, Joint and Back Pain Relief

NDC# 72847-316-20

Distributed by: TopRail Medical Products Glencoe, IL www.toprailmedical.com Made in the USA